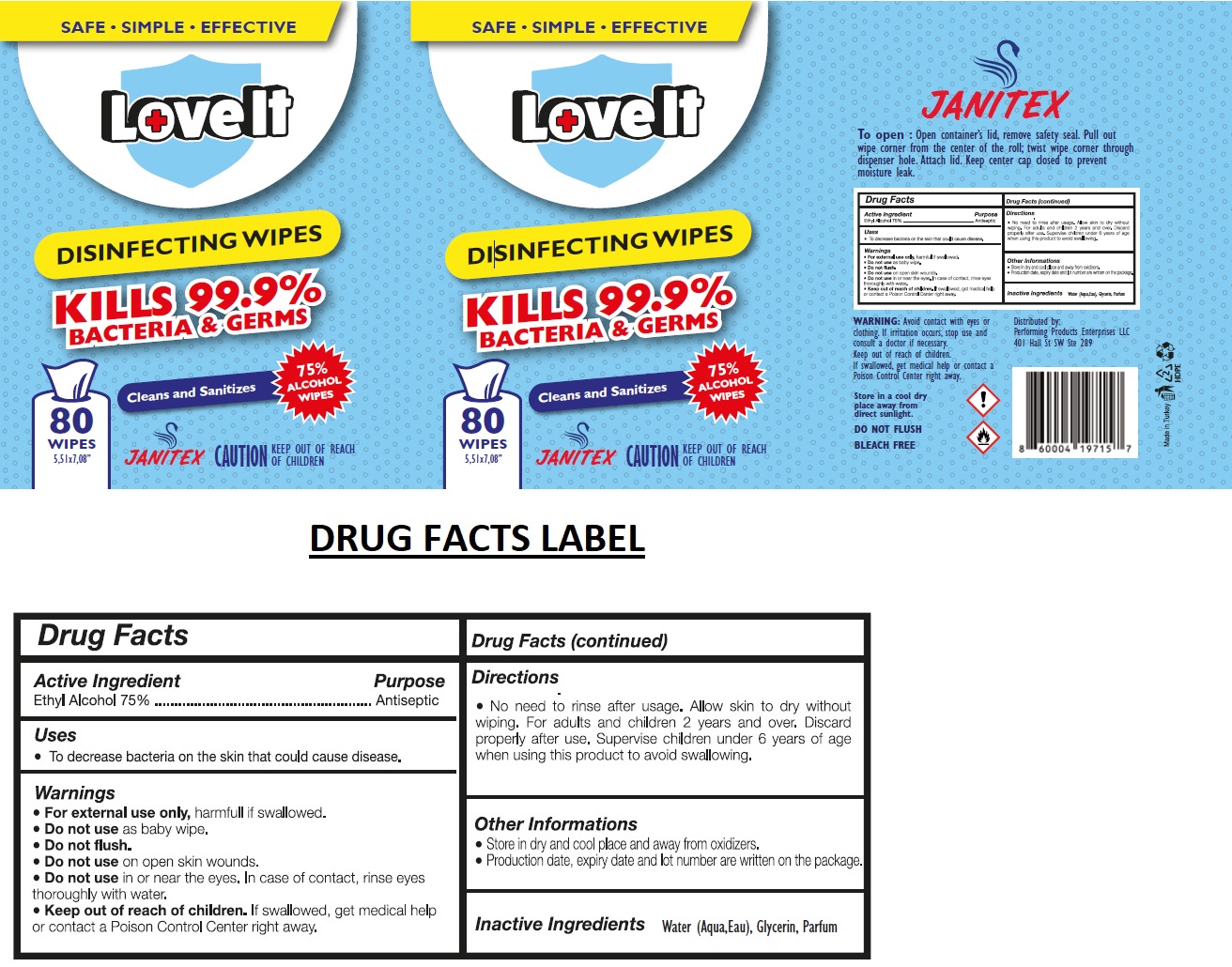 DRUG LABEL: LOVEIT-JANITEX DISINFECTING WIPES 75% ALCOHOL
NDC: 79519-022 | Form: CLOTH
Manufacturer: Pacific Health Systems Inc.
Category: otc | Type: HUMAN OTC DRUG LABEL
Date: 20210209

ACTIVE INGREDIENTS: ALCOHOL 75 mL/100 mL
INACTIVE INGREDIENTS: WATER; GLYCERIN

LOVEIT-JANITEX DISINFECTING WIPES 75% ALCOHOL

Active Ingredient

Ethyl Alcohol 75%

Purpose

Antiseptic

Uses

• To decrease bacteria on the skin that could cause disease.

Warnings

• For external use only, harmful if swallowed.
• Do not use as baby wipe.
• Do not flush.
• Do not use on open skin wounds.
• Do not use in or near the eyes. In case of contact, rinse eyes thoroughly with water.

• Keep out of reach of children. If swallowed, get medical help or contact a Poison Control Center right away.

Directions

• No need to rinse after usage. Allow skin to dry without wiping. For adults and children 2 years and over. Discard properly after use. Supervise children under 6 years of age when using this product to avoid swallowing.

Other Information

• Store in dry and cool place and away from oxidizers.

• Production date, expiry date and lot number are written on the package.

Inactive Ingredients

Water (Aqua, Eau), Glycerin, Parfum

SAFE • SIMPLE • EFFECTIVE

KILLS 99.9% BACTERIA & GERMS

Cleans and Sanitizes

75% ALCOHOL WIPES

To open : Open container's lid, remove safety seal. Pull out wipe corner from the center of the roll; twist wipe corner through dispenser hole. Attach lid. Keep center cap closed to prevent moisture leak.

WARNING: Avoid contact with eyes or clothing. If irritation occurs, stop use and consult a doctor if necessary.

Keep out of reach of children.

If swallowed, get medical help or contact a Poison Control Center right away.

Store in a cool dry place away from direct sunlight.

DO NOT FLUSH

BLEACH FREE

Distributed by:

Performing Products Enterprises LLC

401 Hall St SW Ste 289

Made in Turkey